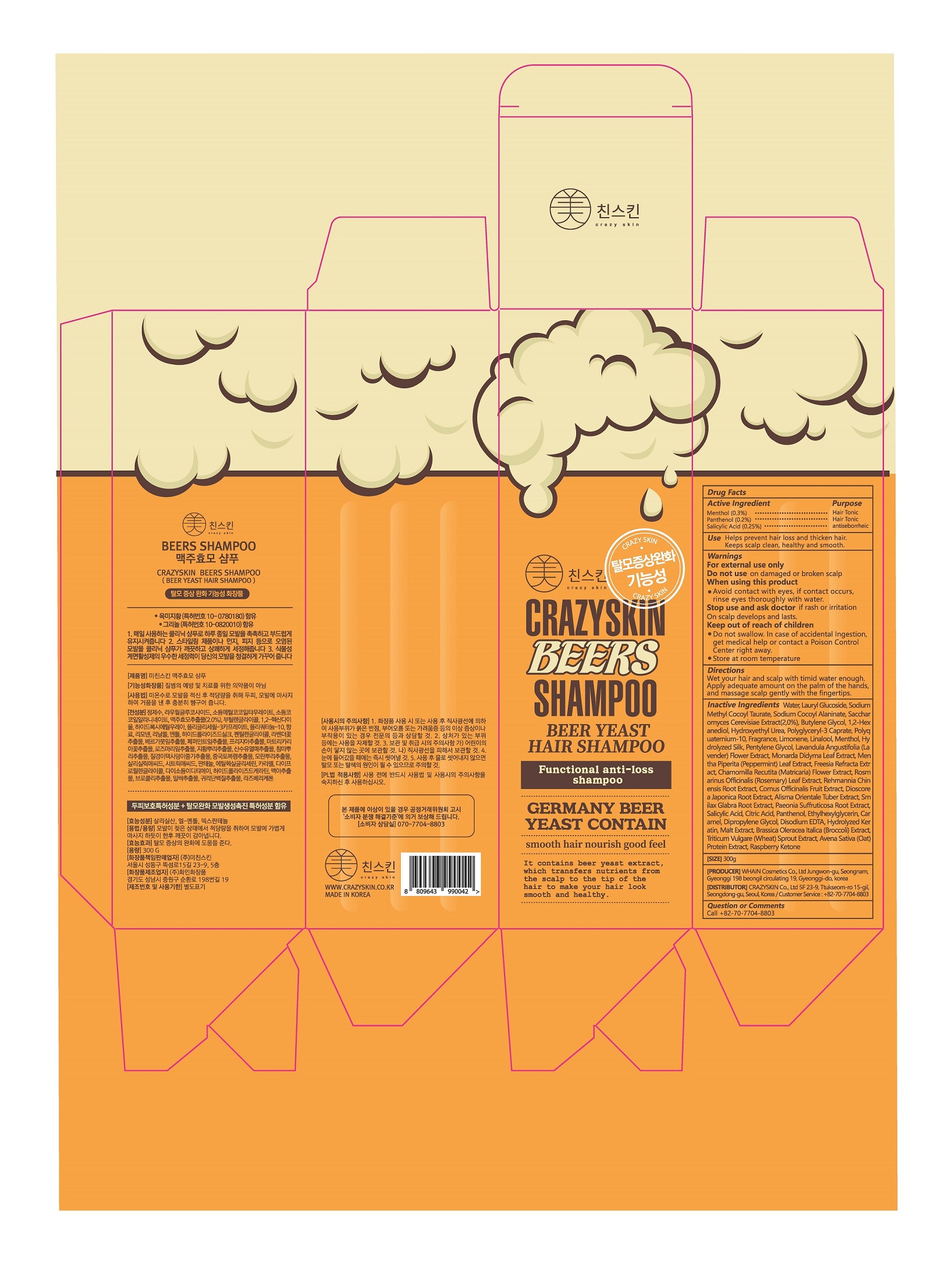 DRUG LABEL: CRAZYSKIN BEERS
NDC: 73643-0001 | Form: SHAMPOO
Manufacturer: Crazy Skin Co., Ltd.
Category: otc | Type: HUMAN OTC DRUG LABEL
Date: 20200228

ACTIVE INGREDIENTS: LEVOMENTHOL 0.3 g/100 g; SALICYLIC ACID 0.25 g/100 g; DEXPANTHENOL 0.2 g/100 g
INACTIVE INGREDIENTS: WATER

ACTIVE INGREDIENT

L-menthol, dexpanthenol, salicylic acid

INACTIVE INGREDIENT

Water, lauryl glucoside, sodium methyl cocoyl taurate, etc

PURPOSE

Helps prevent hair loss and thicken hair, keeps scalp clean, healthy and smooth

do not use on damaged or broken scalp

when using this product

avoid contact with eyes, if contact occurs, rinse eyes thoroughly with water

stop use and ask doctor if rash or irritation on scalp develops and lasts

Keep Out of Reach of Children

DOSAGE AND ADMINISTRATION

wet your hair and scalp with timid water enough

apply adequate amount on the palm of the hands, and massage scalp gently with the fingertips

INDICATIONS AND USAGE

Helps prevent hair loss and thicken hair,

Keep scalp clean, healthy and smooth